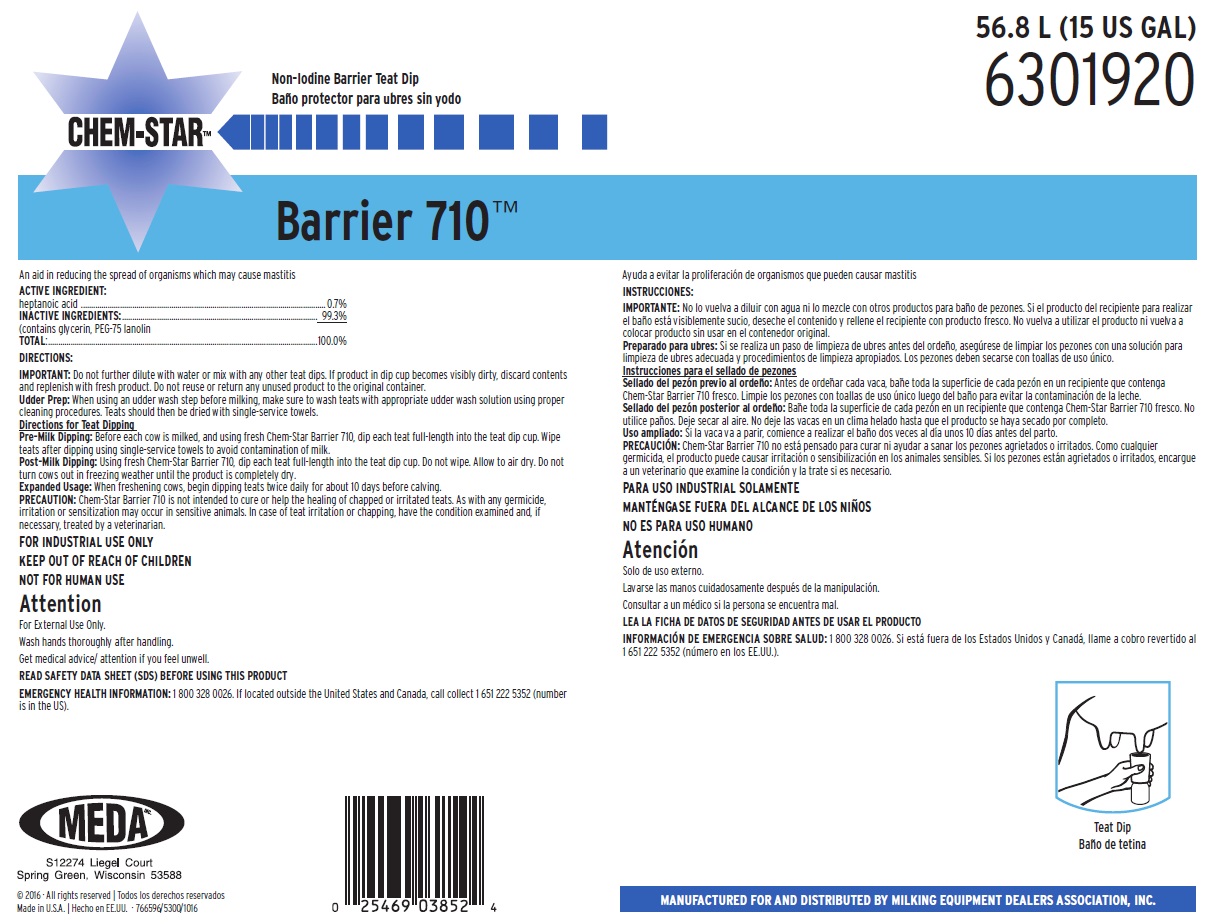 DRUG LABEL: Chem-Star Barrier 710
NDC: 59511-446 | Form: SOLUTION
Manufacturer: MEDA Inc.
Category: animal | Type: OTC ANIMAL DRUG LABEL
Date: 20191022

ACTIVE INGREDIENTS: HEPTANOIC ACID 7 mg/1 mL
INACTIVE INGREDIENTS: GLYCERIN; PEG-75 LANOLIN

SAFE HANDLING WARNING

FOR INDUSTRIAL USE ONLY

KEEP OUT OF REACH OF CHILDREN

NOT FOR HUMAN USE

Attention

For External Use Only.

Wash hands thoroughly after handling.

Get medical advice/attention if you feel unwell.

DIRECTIONS:

IMPORTANT: Do not further dilute with water or mix with any other teat dips. If product in dip cup becomes visibly dirty, discard contents and replenish with fresh product. Do not reuse or return any unused product to the original container.

Udder Prep: When using an udder wash step before milking, make sure to wash teats with appropriate udder wash solution using proper cleaning procedures. Teats should then be dried with single-service towels.

Directions for Teat Dipping

Pre-Milk Dipping: Before each cow is milked, and using fresh Chem-Star Barrier 710, dip each teat full-length into the teat dip cup. Wipe teats after dipping using single-service towels to avoid contamination of milk.

Post-Milk Dipping: Using fresh Chem-Star Barrier 710, dip each teat full-length into the teat dip cup. Do not wipe. Allow to air dry. Do not turn cows out in freezing weather until the product is completely dry.

Expanded Usage: When freshening cows, begin dipping teats twice daily for about 10 days before calving.

PRECAUTION: Chem-Star Barrier 710 is not intended to cure or help the healing of chapped or irritated teats. As with any germicide, irritation or sensitization may occur in sensitive animals. In case of teat irritation or chapping, have the condition examined and, if necessary, treated by a veterinarian.

OTHER SAFETY INFORMATION

READ SAFETY DATA SHEET (SDS) BEFORE USING THIS PRODUCT

EMERGENCY HEALTH INFORMATION: 1 800 328 0026. If located outside the United States and Canada, call collect 1 651 222 5352 (number is in the US).

Principal Display Panel and Representative Label

CHEM-STAR Barrier 710

Non-Iodine Barrier Teat Dip

An Aid in Reducing the Spread of Organisms Which May Cause Mastitis

ACTIVE INGREDIENT:

heptanoic acid............................................................ 0.7%

INACTIVE INGREDIENTS:........................................... 99.3%

(contains glycerin, PEG-75 lanolin

TOTAL:......................................................................100.0%

MEDA
S12274 Liegel Court
Spring Green, Wisconsin 53588

MANUFACTURED FOR AND DISTRIBUTED BY MILKING EQUIPMENT DEALERS ASSOCIATION, INC.

© 2016 · All rights reserved

Made in U.S.A. • 766596/5300/1016